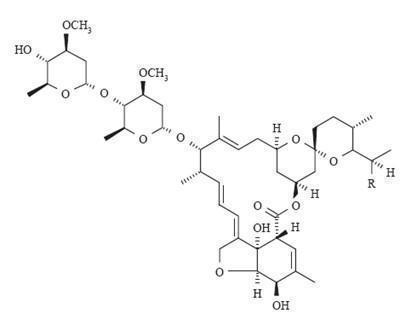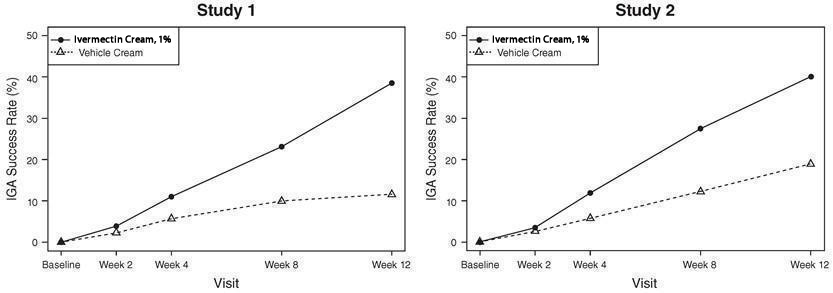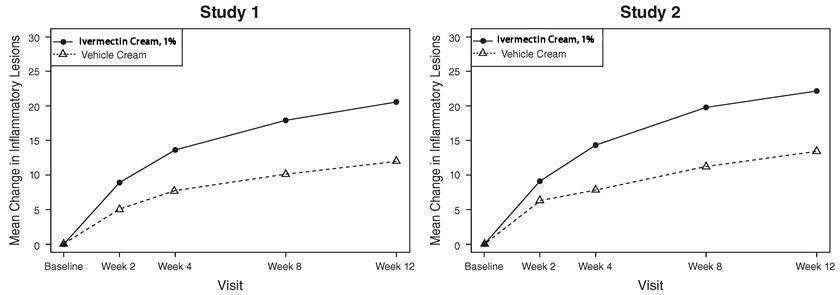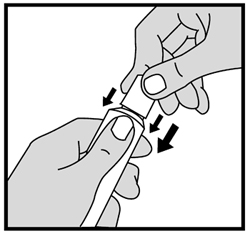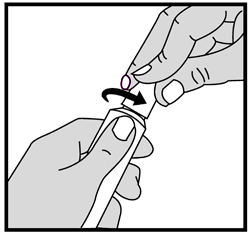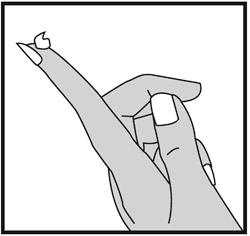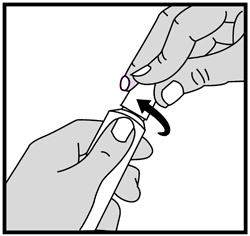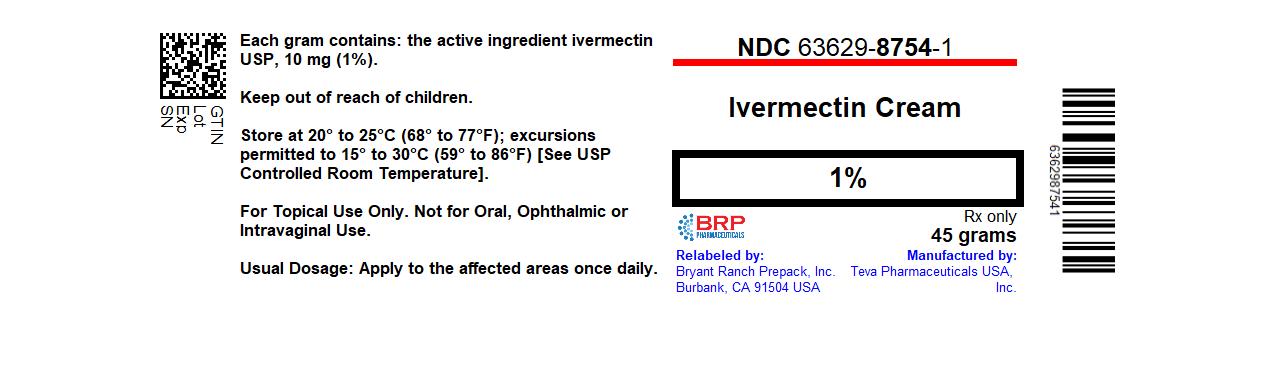 DRUG LABEL: Ivermectin
NDC: 63629-8754 | Form: CREAM
Manufacturer: Bryant Ranch Prepack
Category: prescription | Type: HUMAN PRESCRIPTION DRUG LABEL
Date: 20231030

ACTIVE INGREDIENTS: IVERMECTIN 10 mg/1 g
INACTIVE INGREDIENTS: BENZYL ALCOHOL; ANHYDROUS CITRIC ACID; CARBOMER HOMOPOLYMER TYPE C (ALLYL PENTAERYTHRITOL CROSSLINKED); DIISOPROPYL ADIPATE; EDETATE DISODIUM; HEXYLENE GLYCOL; METHYLPARABEN; OLEYL ALCOHOL; POLYSORBATE 80; PROPYLPARABEN; WATER; SODIUM CITRATE, UNSPECIFIED FORM; SODIUM HYDROXIDE; SORBITAN TRISTEARATE

HIGHLIGHTS OF PRESCRIBING INFORMATION

These highlights do not include all the information needed to use IVERMECTIN CREAM safely and effectively. See full prescribing information for IVERMECTIN CREAM.
IVERMECTIN cream, 1%, for topical use
Initial U.S. Approval: 1996

1 INDICATIONS AND USAGE

Ivermectin cream, 1% is indicated for the treatment of inflammatory lesions of rosacea. (1)

2 DOSAGE AND ADMINISTRATION

- Apply to the affected areas once daily. (2)
- Not for oral, ophthalmic or intravaginal use. (2)

3 DOSAGE FORMS AND STRENGTHS

Cream, 1%, supplied in tubes of 45 g. (3)

4 CONTRAINDICATIONS

None. (4)

6 ADVERSE REACTIONS

In controlled clinical trials with ivermectin cream the most common adverse reactions (incidence less than or equal to 1 %) included skin burning sensation and skin irritation. (6.1)

To report SUSPECTED ADVERSE REACTIONS, contact Teva Pharmaceuticals USA, Inc. at 1-866-832-8537 or FDA at 1-800-FDA-1088 or www.fda.gov/medwatch.

FULL PRESCRIBING INFORMATION

1 INDICATIONS AND USAGE

Ivermectin cream, 1% is indicated for the treatment of inflammatory lesions of rosacea.

2 DOSAGE AND ADMINISTRATION

Apply to the affected areas of the face once daily. Use a pea-size amount for each area of the face (forehead, chin, nose, each cheek) that is affected. Spread as a thin layer, avoiding the eyes and lips.

Ivermectin cream is not for oral, ophthalmic, or intravaginal use.

3 DOSAGE FORMS AND STRENGTHS

Cream, 1%.

Each gram of ivermectin cream contains 10 mg of ivermectin, USP in a white to pale yellow cream base. Ivermectin cream is supplied in tubes of 45 g.

4 CONTRAINDICATIONS

None.

6 ADVERSE REACTIONS

6.1 Clinical Trials Experience

Because clinical trials are conducted under widely varying conditions, adverse reaction rates observed in the clinical trials of a drug cannot be directly compared to rates in the clinical trials of another drug and may not reflect the rates observed in practice.

During clinical trials, 2,047 subjects with inflammatory lesions of rosacea received ivermectin cream once daily. A total of 1,555 subjects were treated once daily for more than 12 weeks, and 519 for approximately one year.

Adverse reactions, reported in less than or equal to 1% of subjects treated with ivermectin cream for at least 3 months in vehicle-controlled clinical trials, included skin burning sensation and skin irritation.

6.2 Postmarketing Experience

Because adverse reactions are reported voluntarily from a population of uncertain size, it is not always possible to reliably estimate their frequency or establish a causal relationship to drug exposure. Local adverse reactions: contact dermatitis and allergic dermatitis.

7 DRUG INTERACTIONS

In vitro studies have shown that ivermectin cream, at therapeutic concentrations, neither inhibits nor induces cytochrome P450 (CYP450) enzymes.

8 USE IN SPECIFIC POPULATIONS

8.1 Pregnancy

Pregnancy Category C.

There are no adequate and well-controlled studies in pregnant women. Ivermectin cream should be used during pregnancy only if the potential benefit justifies the potential risk to the fetus.

Note: The animal multiples of human exposure calculations were based on AUC comparisons. The maximum topical human dose (MTHD) of ivermectin cream is 1 g applied once daily.

Systemic embryofetal development studies were conducted in rats and rabbits. Oral doses of 1.5 mg/kg/day, 4 mg/kg/day, and 12 mg/kg/day ivermectin were administered during the period of organogenesis (gestational days 6 to 17) to pregnant female rats. Maternal death occurred at 12 mg/kg/day (1909X MTHD). Cleft palate occurred in the fetuses from the 12 mg/kg/day (1909X MTHD) group. No treatment related effects on embryofetal toxicity or teratogenicity were noted at 4 mg/kg/day (708X MTHD). Oral doses of 0.5 mg/kg/day, 1.5 mg/kg/day, 2.5 mg/kg/day, 3.5 mg/kg/day, and 4.5 mg/kg/day ivermectin were administered during the period of organogenesis (gestational days 7 to 20) to pregnant female rabbits. Maternal death occurred at doses greater than or equal to 2.5 mg/kg/day (72X MTHD). Carpal flexure occurred in the fetuses from the 4.5 mg/kg/day (354X MTHD) group. Fetal weight decrease was noted at 3.5 mg/kg/day (146X MTHD). No treatment related effects on embryofetal toxicity were noted at 2.5 mg/kg/day (72X MTHD) and no treatment related effects on teratogenicity were noted at 3.5 mg/kg/day (146X MTHD).

A pre- and post-natal development study was conducted in rats. Oral doses of 1 mg/kg/day, 2 mg/kg/day, and 4 mg/kg/day ivermectin were administered to pregnant female rats during gestational days 6 to 20 and lactation days 2 to 20. Neonatal death occurred at doses greater than or equal to 2 mg/kg/day. Behavior development of newborn rats was adversely affected at all doses.

8.3 Nursing Mothers

Following oral administration, ivermectin is excreted in human milk in low concentrations. Excretion in human milk following topical administration has not been evaluated. In oral studies in rats, ivermectin was excreted in the milk of nursing mothers and neonatal toxicity was observed in the litters. The blood-brain barrier in neonatal rats may not be fully developed at birth. Because of the potential for serious adverse reactions from ivermectin cream in nursing infants, a decision should be made whether to discontinue nursing or to discontinue the drug, taking into account the importance of the drug to the mother.

8.4 Pediatric Use

Safety and effectiveness of ivermectin cream in pediatric patients have not been established.

8.5 Geriatric Use

Of the 1,371 subjects in the two pivotal clinical studies of ivermectin cream, 170 (12.4%) were 65 and over, while 37 (2.7%) were 75 and over. No overall differences in safety or effectiveness were observed between these subjects and younger subjects, and other reported clinical experience has not identified differences in responses between the elderly and younger patients, but greater sensitivity of some older individuals cannot be ruled out.

10 OVERDOSAGE

In accidental or significant exposure to unknown quantities of veterinary formulations of ivermectin in humans, either by ingestion, inhalation, injection, or exposure to body surfaces, the following adverse effects have been reported most frequently: rash, edema, headache, dizziness, asthenia, nausea, vomiting, and diarrhea. Other adverse effects that have been reported include: seizure, ataxia, dyspnea, abdominal pain, paresthesia, urticaria, and contact dermatitis.

In case of accidental ingestion, supportive therapy, if indicated, should include parenteral fluids and electrolytes, respiratory support (oxygen and mechanical ventilation if necessary) and pressor agents if clinically significant hypotension is present. Induction of emesis and/or gastric lavage as soon as possible, followed by purgatives and other routine anti-poison measures, may be indicated if needed to prevent absorption of ingested material.

11 DESCRIPTION

Ivermectin cream, 1% is a white to pale yellow hydrophilic cream. Each gram of ivermectin cream contains 10 mg of ivermectin, USP. It is intended for topical use.

Ivermectin, USP is a semi-synthetic derivative isolated from the fermentation of Streptomyces avermitilis that belongs to the avermectin family of macrocyclic lactones.

Ivermectin, USP is a mixture containing not less than 95.0 % and not more than 102.0 % of 5-O-demethyl-22,23-dihydroavermectin A1a plus 5-O-demethyl-25-de(1-methylpropyl)-25-(1-methylethyl)-22,23-dihydroavermectin A1a, generally referred to as 22,23-dihydroavermectin B1a and B1b or H2B1a and H2B1b, respectively; and the ratio (calculated by area percentage) of component H2B1a/(H2B1a + H2B1b)) is not less than 90.0 %.

The respective molecular formulas of H2B1a and H2B1b are C48H74O14 and C47H72O14 with molecular weights of 875.10 and 861.07 respectively.

The structural formulas are:

Component H2B1a: R = C2H5, Component H2B1b: R = CH3.

Ivermectin cream, 1% contains the following inactive ingredients: benzyl alcohol, citric acid anhydrous, carbomer homopolymer type c, di-isopropyl adipate, edetate disodium, hexylene glycol, methylparaben, oleyl alcohol, polysorbate 80, propylparaben, purified water, sodium citrate, sodium hydroxide, and sorbitan tristearate.

12 CLINICAL PHARMACOLOGY

12.1 Mechanism of Action

The mechanism of action of ivermectin cream in treating rosacea lesions is unknown.

12.2 Pharmacodynamics

Cardiac Electrophysiology

At therapeutic doses, ivermectin cream is not expected to prolong QTc interval.

12.3 Pharmacokinetics

Absorption

The absorption of ivermectin from ivermectin cream was evaluated in a clinical trial in 15 adult male and female subjects with severe papulopustular rosacea applying 1 g ivermectin cream, 1% once daily. At steady state (after 2 weeks of treatment), the highest mean ± standard deviation) plasma concentrations of ivermectin peaked (Tmax) at 10 ± 8 hours post-dose, the maximum concentration (Cmax) was 2.10 ± 1.04 ng/mL (range: 0.69 to 4.02 ng/mL) and the area under the concentration curve (AUC0-24hr) was 36.14 ± 15.56 ng.hr/mL (range: 13.69 to 75.16 ng•hr/mL). In addition, systemic exposure assessment in longer treatment duration (Phase 3 studies) showed that there was no plasma accumulation of ivermectin over the 52-week treatment period.

Distribution

An in vitro study demonstrated that ivermectin is greater than 99% bound to plasma proteins and is bound primarily to human serum albumin. No significant binding of ivermectin to erythrocytes was observed.

Metabolism

In vitro studies using human hepatic microsomes and recombinant CYP450 enzymes have shown that ivermectin is primarily metabolized by CYP3A4. In vitro studies show that ivermectin at therapeutic concentrations does not inhibit the CYP450 isoenzymes 1A2, 2A6, 2B6, 2C8, 2C9, 2C19, 2D6, 2E1, 3A4 or 4A11, or induce 1A2, 2B6, 2C9 or 3A4.

Excretion

The apparent terminal half-life averaged 6.5 days (mean ± standard deviation: 155± 40 hours, range 92 to 238 hours) in patients receiving a once daily cutaneous application of ivermectin cream for 28 days.

13 NONCLINICAL TOXICOLOGY

13.1 Carcinogenesis, Mutagenesis, Impairment of Fertility

In a 2-year dermal mouse carcinogenicity study, ivermectin was administered to CD-1 mice at topical doses of 1, 3, and 10 mg/kg/day (0.1%, 0.3% and 1% ivermectin cream applied at 2 mL/kg/day). No drug-related tumors were noted in this study up to the highest dose evaluated in this study of 10 mg/kg/day (747X maximum topical human dose (MTHD)).

In a 2-year oral rat carcinogenicity study, ivermectin was administered to Wistar rats at gavage doses of 1 mg/kg/day, 3 mg/kg/day, and 9 mg/kg/day. A statistically significant increase in the incidence of hepatocellular adenoma was noted in males treated with 9 mg/kg/day (1766X MTHD) ivermectin. The clinical relevance of this finding is unknown. No drug-related tumors were noted in females up to the highest dose evaluated in this study of 9 mg/kg/day (1959X MTHD). No drug-related tumors were noted in males at doses less than or equal to 3 mg/kg/day (599X MTHD).

Ivermectin revealed no evidence of genotoxic potential based on the results of two in vitro genotoxicity tests (the Ames test and the L5178Y/TK+/- mouse lymphoma assay) and one in vivo genotoxicity test (rat micronucleus assay).

In a fertility study, oral doses of 0.1 mg/kg/day, 1 mg/kg/day, and 9 mg/kg/day ivermectin were administered to male and female rats. Mortality occurred at 9 mg/kg/day (1027X MTHD). The precoital period was generally prolonged at 9 mg/kg/day. No treatment related effects on fertility or mating performance were noted at doses less than or equal to 1 mg/kg/day (68X MTHD).

14 CLINICAL STUDIES

Ivermectin cream applied once daily at bedtime was evaluated in the treatment of inflammatory lesions of rosacea in two randomized, double-blind, vehicle-controlled clinical trials, which were identical in design. The trials were conducted in 1,371 subjects aged 18 years and older who were treated once daily for 12 weeks with either ivermectin cream or vehicle cream.

Overall, 96% of subjects were Caucasian and 67% were female. Using the 5-point Investigator Global Assessment (IGA) scale (0=clear, 1=almost clear, 2=mild, 3=moderate, 4=severe), 79% of subjects were scored as moderate (IGA=3) and 21% scored as severe (IGA=4) at baseline.

The co-primary efficacy endpoints in both pivotal trials were the success rate based on the IGA outcome (percentage of subjects “clear” and “almost clear”) and absolute change from baseline in inflammatory lesion counts at Week 12. Table 1 presents the co-primary efficacy results at Week 12. Ivermectin cream was more effective than vehicle cream on the co-primary efficacy endpoints starting from 4 weeks of treatment in both studies, see Figures 1 through 4.

Table 1: Co-Primary Efficacy Results at Week 12
 | Study 1 |  | Study 2
 | Ivermectin | Vehicle | Ivermectin | Vehicle
 | Cream (N=451) | Cream (N=232) | Cream (N=459) | Cream (N=229)
Investigator Global Assessment:
Number (%) of Subjects Clear or Almost Clear | 173 (38.4%) | 27 (11.6%) | 184 (40.1%) | 43 (18.8%)
Inflammatory Lesion Counts:
Mean Absolute (%) Change from Baseline | 20.5 (64.9%) | 12.0 (41.6%) | 22.2 (65.7%) | 13.4 (43.4%)

Figures 1 and 2: IGA Success Rates Over Time

Figures 3 and 4: Mean Absolute Change in Inflammatory Lesion Counts from Baseline Over Time

16 HOW SUPPLIED/STORAGE AND HANDLING

Ivermectin cream, 1% is a white to pale yellow cream, supplied in a laminated tube with a child resistant cap in the following size:

45 gram – NDC: 63629-8754-1

Storage

Store at 20°C to 25°C (68°F to 77°F); excursions permitted between 15°C and 30°C (59°F and 86°F) [See USP Controlled Room Temperature].

Repackaged/Relabeled by:

Bryant Ranch Prepack, Inc.

Burbank, CA 91504

17 PATIENT COUNSELING INFORMATION

Advise the patient to read the FDA-approved patient labeling (Instructions for Use).

Patients using ivermectin cream should receive the following instruction:

Keep out of reach of children.

Teva Pharmaceuticals USA, Inc.
North Wales, PA 19454

Revised – January 2019

INSTRUCTION FOR USE

Ivermectin (eye" ver mek' tin) Cream, 1%

Important: Ivermectin cream is for use on the face only. Do not use ivermectin cream in your eyes, mouth or vagina.

Read and follow the steps below so that you use ivermectin cream correctly:

1. Open the tube of ivermectin cream by gently pressing down on the child resistant cap and twist in the direction of the arrow (counterclockwise) as shown below. See Figures A and B. To avoid spilling, do not squeeze the tube while opening or closing.

Figure A
Figure B

2. To apply ivermectin cream to your face, squeeze a pea-sized amount of ivermectin cream from the tube onto your fingertip. See Figure C.

Figure C

3. Apply ivermectin to the affected areas of your face once a day. Use a pea-sized amount of ivermectin cream for each area of your face (forehead, chin, nose, each cheek) that is affected. Spread the cream smoothly and evenly in a thin layer. Avoid contact with your eyes and lips.

4. To close ivermectin cream, gently press down on the child resistant cap and twist to the right (clockwise). See Figure D.

Figure D

How should I store ivermectin cream?

- Store ivermectin cream at room temperature between 68°F to 77°F (20°C to 25°C).

Keep ivermectin cream out of the reach of children.

This Instructions for Use has been approved by the U.S. Food and Drug Administration.

Teva Pharmaceuticals USA, Inc.
North Wales, PA 19454

Revised – January 2019

PACKAGE LABEL

Ivermectin 10 mg/g Cream #45